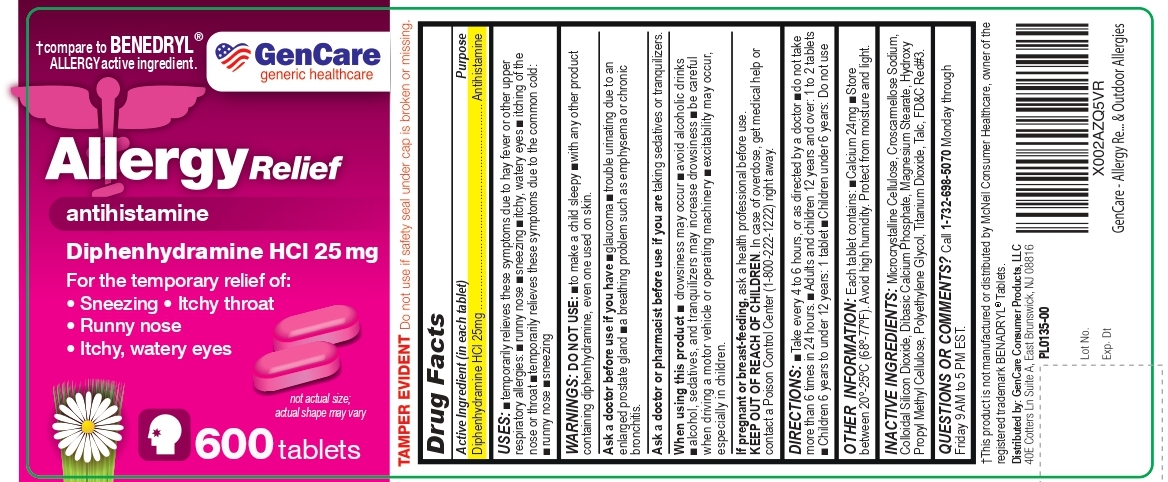 DRUG LABEL: Allergy Relief
NDC: 72090-029 | Form: TABLET
Manufacturer: Pioneer Life Sciences, LLC
Category: otc | Type: HUMAN OTC DRUG LABEL
Date: 20251223

ACTIVE INGREDIENTS: DIPHENHYDRAMINE HYDROCHLORIDE 25 mg/1 1
INACTIVE INGREDIENTS: CELLULOSE, MICROCRYSTALLINE; CROSCARMELLOSE SODIUM; ANHYDROUS DIBASIC CALCIUM PHOSPHATE; SILICON DIOXIDE; MAGNESIUM STEARATE; TALC; TITANIUM DIOXIDE; POLYETHYLENE GLYCOL, UNSPECIFIED; FD&C RED NO. 3; HYPROMELLOSE, UNSPECIFIED

Active Ingredient (in each tablet)

Diphenhydramine Hcl 25mg

Purpose

Antihistamine

Uses:

- temporarily relieves these symptoms due to hay fever or other upper respiratory allergies:
- runny nose
- sneezing
- itchy, watery eyes
- itching of the nose or throat
- temporarily relieves these symptoms due to the common cold:
- runny nose
- sneezing

Warnings:

DO NOT USE:

- to make a child sleepy
- with any other product containing diphenhydramine, even one used on skin

Ask a doctor before use if you have

- glaucoma
- troble urinating due to an enlarged prostate gland
- a breathing problem such as emphysema or chronic bronchitis

Ask a doctor or pharmacist before use if you are taking sedatives or tranquilizers.

When using this product ■ drowsiness may occur ■avoid alcoholic drinks ■alcohol, sedatives, and tranquilizers may increase drowsiness ■be careful when driving a motor vehicle or operating machinery ■excitability may occur, especially in children.

PREGNANCY OR BREAST FEEDING

If pregnant or breast-feeding, ask a health professional before use.

Keep out of reach of children. In case of overdose, get medical help or contact a Poison Control Center (1-800-222-1222) right away.

DIRECTIONS

■ Take every 4 to 6 hours, or as directed by a doctor

■ do not take more than 6 times in 24 hours.

■Adults and children 12 years and over: Take 1 to 2 tablets

■ Children 6 years to under 12 years: 1 tablet

■Children under 6 years: Do not use

OTHER INFORMATION

Each tablet contains: ■ Calcium 24mg ■Store between 20º-25ºC (68º-77ºF). Avoid high humidity. Protect from moisture and light.

INACTIVE INGREDIENTS

Microcrystalline Cellulose, Croscarmellose Sodium, Colloidal Silicon Dioxide, Dibasic Calcium Phosphate, Magnesium Stearate, Hydroxy Propyl Methyl Cellulose, Polyethylene Glycol, Titanium Dioxide, Talc, FD&C Red#3.

QUESTIONS OR COMMENTS?

Call 1-732-698-5070 Monday through Friday 9 AM to 5 PM EST

†This product is not manufactured or distributed by McNeil Consumer Healthcare, owner of the registered trademark BENADRYL® Tablets.

Distributed by: GenCare Consumer Products, LLC

40E Cotters Ln, Suite A, East Brunswick, New Jersey 08816